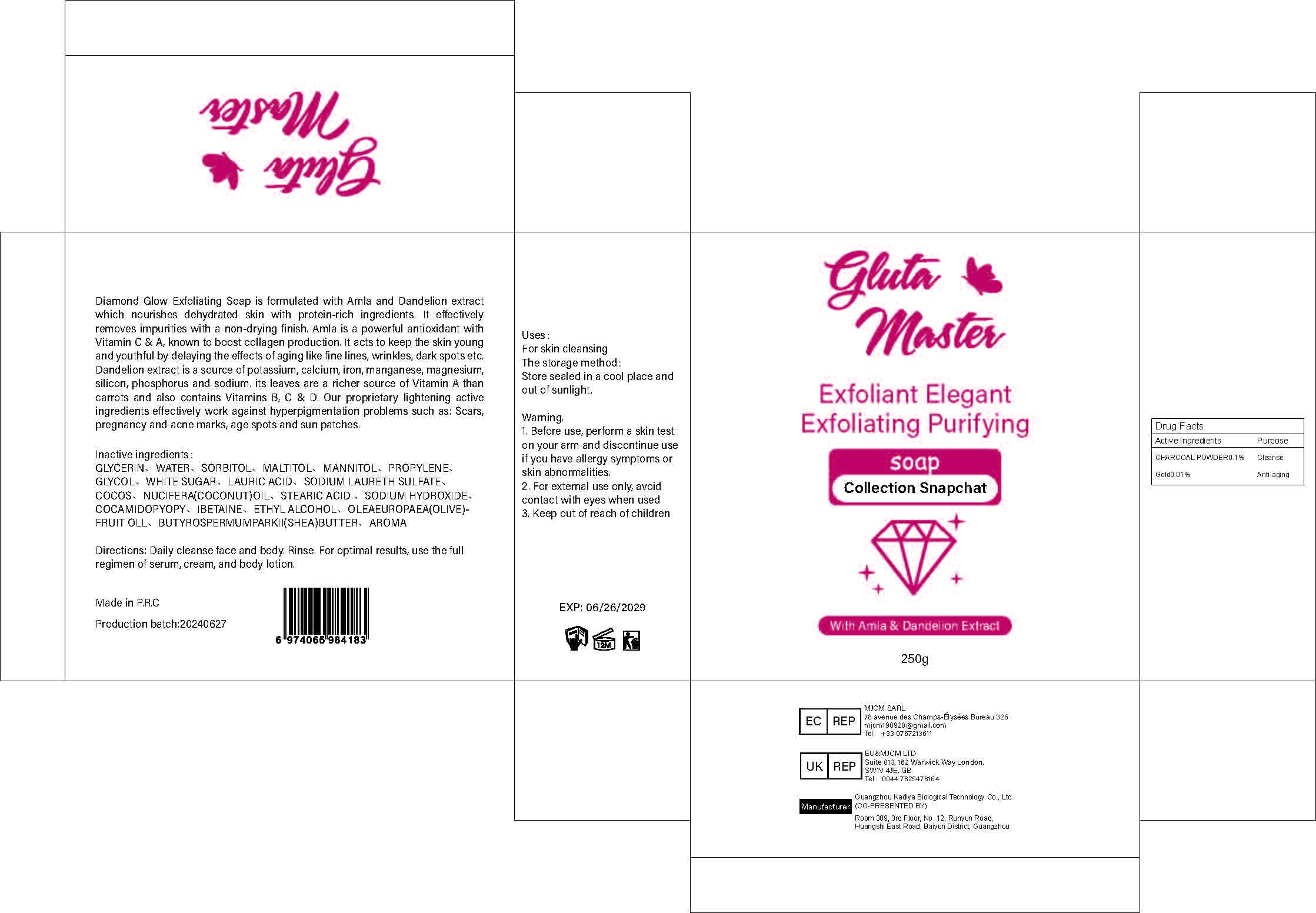 DRUG LABEL: Collection ShineSoap
NDC: 84423-013 | Form: SOAP
Manufacturer: Guangzhou Kadiya Biotechnology Co., Ltd.
Category: otc | Type: HUMAN OTC DRUG LABEL
Date: 20240708

ACTIVE INGREDIENTS: ACTIVATED CHARCOAL 0.25 mg/250 mL; GOLD 0.025 mg/250 mL
INACTIVE INGREDIENTS: SORBITOL; SODIUM LAURETH SULFATE; STEARIC ACID; ALCOHOL; PROPYLENE GLYCOL; GLYCERIN; LAURIC ACID; COCONUT OIL; COCO/OLEAMIDOPROPYL BETAINE; MALTITOL; SODIUM HYDROXIDE; WATER; SUCROSE; MANNITOL

PURPOSE

For skin cleansing
Indications: For skin whitening cleansing exfoliatio

INACTIVE INGREDIENT

GLYCERIN、WATER、SORBITOL、MALTITOL、MANNITOL、PROPYLENE、GLYCOL、WHITE SUGAR、LAURIC ACID、SODIUM LAURETH SULFATE、COCOS、NUCIFERA(COCONUT)OIL、STEARIC ACID 、SODIUM HYDROXIDE、COCAMIDOPYOPY、IBETAINE、ETHYL ALCOHOL、OLEAEUROPAEA(OLIVE)FRUIT OLL、BUTYROSPERMUMPARKII(SHEA)BUTTER、AROMA、CHARCOAL POWDER、Gold

Warning.
1.Before use, perform a skin test on your arm and discontinue use if you have allergy symptoms or skin abnormalities.
2、For external use only, avoid contact with eyes when used
3、Keep out of reach of children

INDICATIONS AND USAGE

For skin cleansing

KEEP OUT OF REACH OF CHILDREN SECTION

DOSAGE AND ADMINISTRATION

Daily cleanse face and body. Rinse. For optimal results, use the fullregimen of serum, cream, and body lotion.

Active Ingredients
CHARCOAL POWDER 0.1%
Gold 0.01%

PACKAGE LABEL

Active Ingredients
CHARCOAL POWDER0.1%
Gold0.01%

Uses：
For skin cleansing
Indications: For skin whitening cleansing exfoliation
The storage method：
Store sealed in a cool place and out of sunlight

Warning.
1.Before use, perform a skin test on your arm and discontinue use if you have allergy symptoms or skin abnormalities.
2、For external use only, avoid contact with eyes when used
3、Keep out of reach of children

Inactive ingredients：
GLYCERIN、WATER、SORBITOL、MALTITOL、MANNITOL、PROPYLENE、GLYCOL、WHITE SUGAR、LAURIC ACID、SODIUM LAURETH SULFATE、COCOS、NUCIFERA(COCONUT)OIL、STEARIC ACID 、SODIUM HYDROXIDE、COCAMIDOPYOPY、IBETAINE、ETHYL ALCOHOL、OLEAEUROPAEA(OLIVE)FRUIT OLL、BUTYROSPERMUMPARKII(SHEA)BUTTER、AROMA、CHARCOAL POWDER、Gold